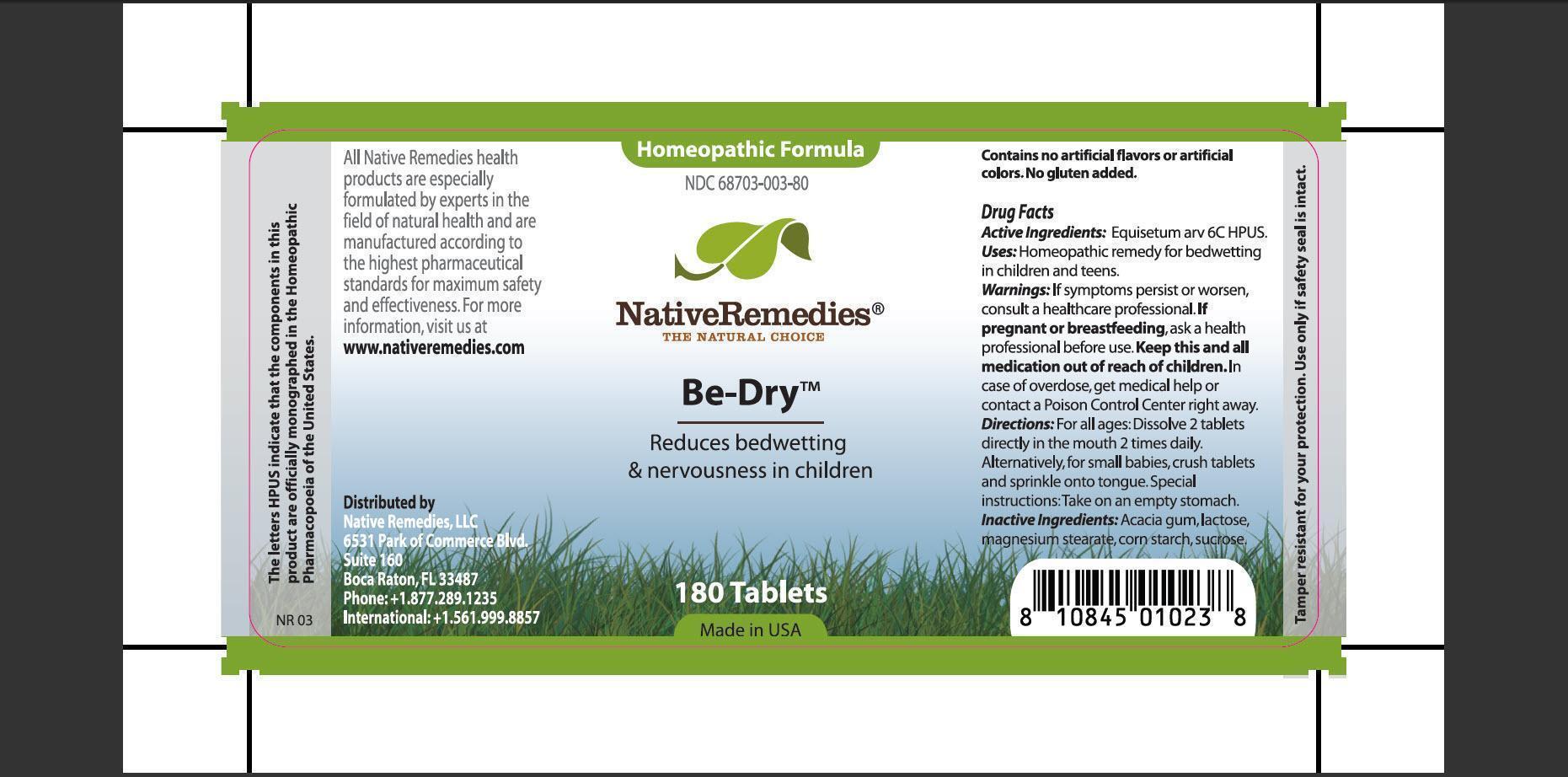 DRUG LABEL: Be-Dry
                
                
                
NDC: 68703-003 | Form: TABLET
Manufacturer: Native Remedies, LLC
Category: homeopathic | Type: HUMAN OTC DRUG LABEL
Date: 20130102

ACTIVE INGREDIENTS: EQUISETUM ARVENSE TOP     6 [hp_C]/1 1
INACTIVE INGREDIENTS: ACACIA; LACTOSE; MAGNESIUM STEARATE; STARCH, CORN; SUCROSE

Be-Dry

PURPOSE

Reduces bedwetting and nervousness in children

Active Ingredients: Equisetum arv 6C HPUS.

INDICATIONS AND USAGE

Uses: Homeopathic remedy for bedwetting in children and teens.

WARNINGS

Warnings: If symptoms persist or worsen, consult a healthcare professional.

PREGNANCY OR BREAST FEEDING

If pregnant or breastfeeding, ask a health professional before use.

KEEP OUT OF REACH OF CHILDREN

Keep this and all medication out of reach of children.

OVERDOSAGE

In case of overdose, get medical help or contact Poison Control Center right away.

DOSAGE AND ADMINISTRATION

Directions: For all ages: Dissolve 2 tablets directly in the mouth 2 times daily. Alternatively, for small babies, crush tablets and sprinkle onto tongue. Special instructions: Take on an empty stomach.

INACTIVE INGREDIENT

Inactive Ingredients: Acacia gum, lactose, magnesium stearate, corn starch, sucrose.

PATIENT COUNSELING INFORMATION

The letters HPUS indicate that the components in this product are officially monographed in the Homeopathic Pharmacopoeia of the United States.

All Native Remedies health products are specially formulated by experts in the field of natural health and are manufactured according to the highest pharmaceutical standards for maximum safety and effectiveness. For more information, visit us at www.nativeremedies.com

Distributed by
Native Remedies, LLC
6531 Park of Commerce Blvd.
Suite 160
Boca Raton, FL 33487
Phone:+1.877.289.1235
International:+1.561.999.8857

Contains no artificial flavors or artificial colors. No gluten added.

STORAGE AND HANDLING

Tamper resistant for your protection. Use only if safety seal is intact.